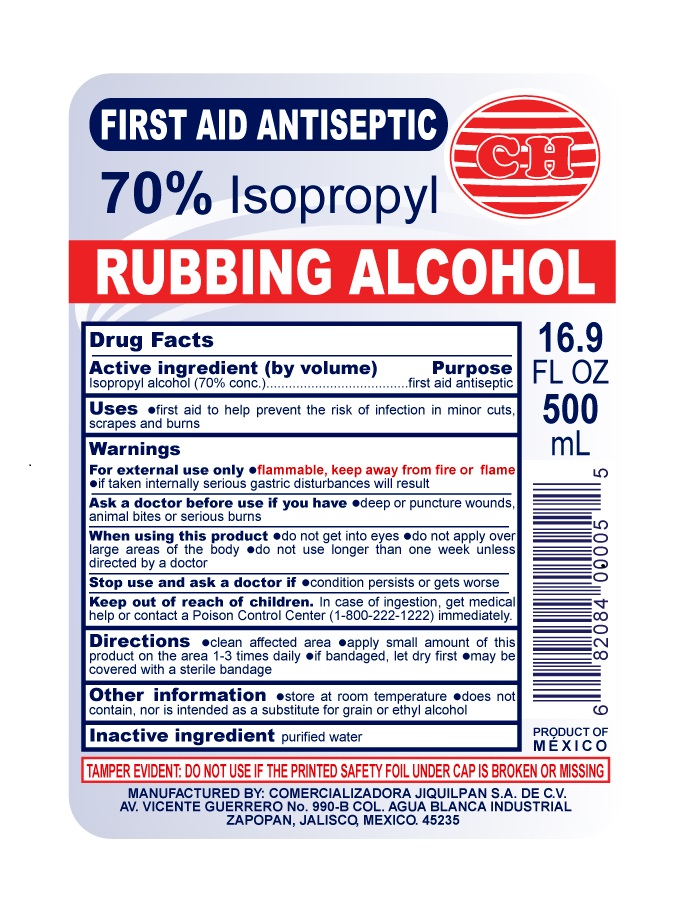 DRUG LABEL: ISOPROPYL RUBBING ALCOHOL
NDC: 15231-200 | Form: LIQUID
Manufacturer: COMERCIALIZADORA JIQUILPAN S.A. DE C.V.
Category: otc | Type: HUMAN OTC DRUG LABEL
Date: 20150817

ACTIVE INGREDIENTS: ISOPROPYL ALCOHOL 350 mL/500 mL
INACTIVE INGREDIENTS: WATER 150 mL/500 mL

Isopropyl Alcohol, Comercializadora Jiquilpan

PACKAGE LABEL

FIRST AID ANTISEPTIC

70% iSOPROPYL

RUBBING ALCOHOL

16.9 FL OZ 500mL

ACTIVE iNGREDIENT

ACTIVE INGREDIENT (BY VOLUME) PURPOSE

ISOPROPYL ALCOHOL 70%CONC.) FIRST AID ANTISEPTIC

USES

USES FIRST AID TO PREVENT THE RISK OF INFECTION IN MINOR CUTS

WARNINGS

FOR EXTERNAL USE ONLY. FLAMMABLE, KEEP AWAY FROM FIRE OR FLAME.

IF TAKEN INTERNALLY SERIOUS GASTRIC DISTURBANCES MAY RESULT.

ASK A DOCTOR BEFORE USE IF YOU HAVE; DEEP OR PUNCTURE WOUNDS, ANIMAL BITES OR SERIOUS BURNS

INACTIVE INGREDIENT

INACTIVE INGREDIENT PURIFIED WATER

TAMPER

TAMPER EVIDENT: DO NOT USE IF THE PRINTED SAFETY FOIL UNDER CAP IS BROKEN OR MISSING

WHEN USING

WHEN USING THIS PRODUCT- DO NOT GET INTO EYES DO NOT APPLY OVER LARGE AREAS OF BODY DO NOT USE LONGER THAN ONE WEEK UNLESS DIRECTED BY A DOCTOR

KEEP OUT OF CHILDREN

KEEP OUT OF REACH OF CHILDREN. IN CASE OF INGESTION, GET MEDICAL HELP OR CONTACT A POISON CONTROL CENTER (1-800-222-1222)IMMEDIATELY.

STOP USE

STOP USE AND ASK A DOCTOR IF-CONDITION PERSISTS OR GETS WORSE

OTHER INFORMATION

OTHER INFORMATION STORE AT ROOM TEMPERATURE-DOES NOT CONTAIN, NOR IIS INTENDED AS A SUBSTITUTE FOR GRAIN OR ETHYL ALCOHOL

Warnings

For external use only -flammable, keep away from fire or flame-if taken internally serious gastric disturbances will result

INDICATIONS AND USAGE

<p>Uses -first aid to help prevent the risk of infection in minor cuts, scrapes and burns.</p>

<p>WARNINGS</p>

<p>For External use only. if taken internallyserious gastric disturbances will result</p>

<p>Ask a doctor before use if you have-deep or puncture wounds, animal bites or serious burns</p>

DOSAGE AND ADMINISTRATION

Directions clean affected area-apply small amount of this product on the area 1-3 times daily -If bandaged, let dry first - may ba covered with a sterile bandage